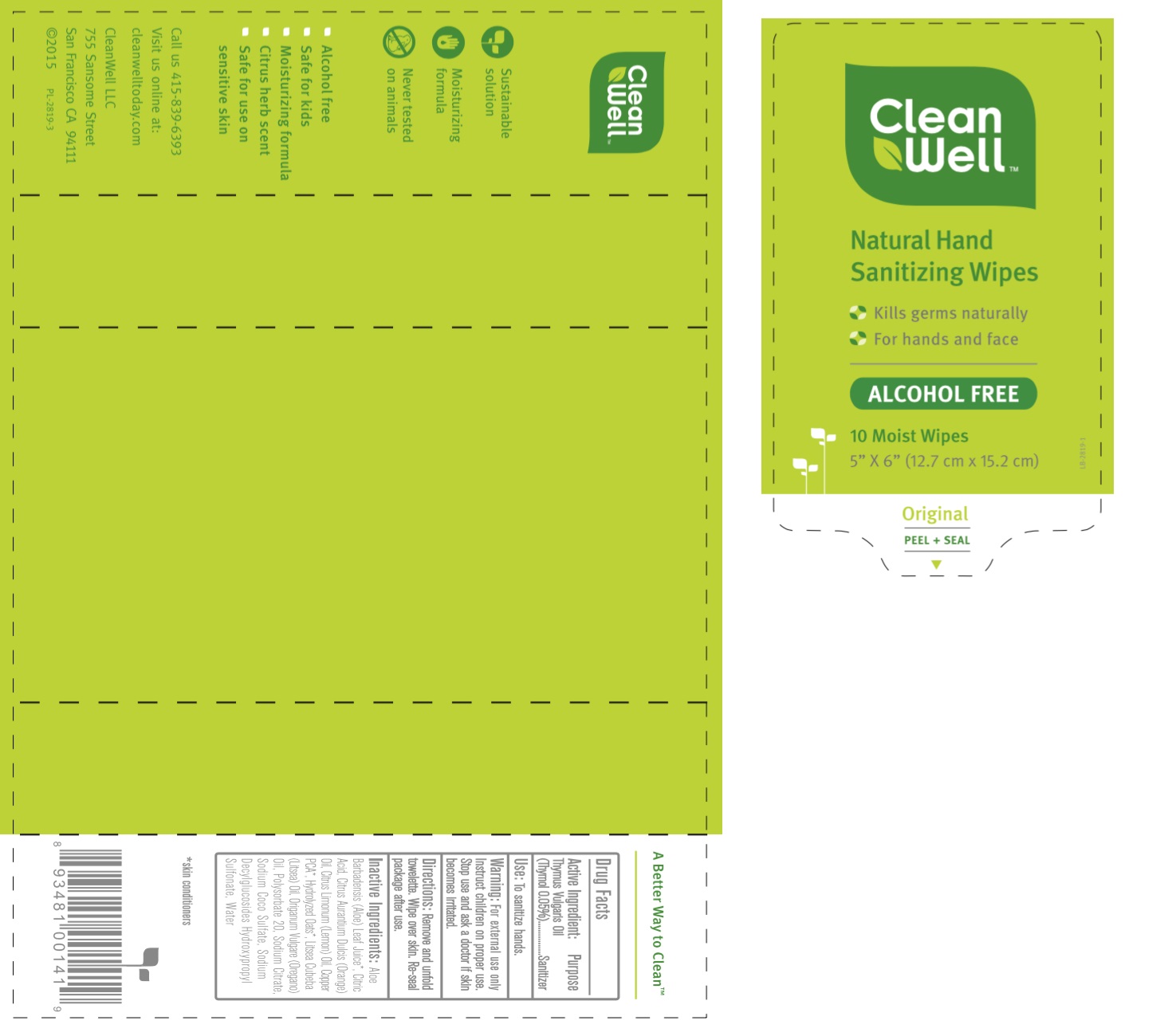 DRUG LABEL: CleanWell Natural Original Hand Sanitizer Wipes
NDC: 28107-002 | Form: CLOTH
Manufacturer: CleanWell, LLC
Category: otc | Type: HUMAN OTC DRUG LABEL
Date: 20180403

ACTIVE INGREDIENTS: THYMOL 0.0005 kg/1 kg
INACTIVE INGREDIENTS: THYME OIL 0.0003 kg/1 kg; OREGANO LEAF OIL 0.0001 kg/1 kg; ORANGE OIL 0.0005 kg/1 kg; NERAL 0.0018 kg/1 kg; LEMON OIL 0.00075 kg/1 kg; SODIUM DECYLGLUCOSIDES HYDROXYPROPYLSULFONATE 0.0016 kg/1 kg; SODIUM COCO-SULFATE 0.0032 kg/1 kg; ANHYDROUS CITRIC ACID 0.00046 kg/1 kg; SODIUM CITRATE 0.0007 kg/1 kg; COPPER 0.00008 kg/1 kg; AMINO ACIDS, OAT 0.001 kg/1 kg; ALOE VERA LEAF 0.0025 kg/1 kg; WATER 0.98651 kg/1 kg

CleanWell Natural Original Hand Sanitizing Wipes

Active Ingredient:

Thymus Vulgaris Oil (Thymol 0.05%)

Purpose

Sanitizer

Use:

To sanitize hands.

WARNINGS

For external use only

Instruct children on proper use.

Stop use and ask a doctor if skin becomes irritated

Directions:

Apply thoroughly to hands and face as desired. Close lid between uses to retain moisture. Do not flush wipes. To Dispense: Lift tab at front of lid to open. Pull up corner of center sheet and thread through dispenser slit in lid. Pull out exposed wipe at 45 angle and snap off. The next wipe is ready for dispensing.

Inactive Ingredients:

Aloe Barbadensis (Aloe) Leaf Juice*, Citric Acid, Citrus Aurantium Dulcis (Orange) Oil, Copper PCA*, Hydrolyzed Oats*, Origanum Vulgare (Oregano) Oil, Sodium Citrate, Sodium Coco Sulfate, Sodium Decylglucosides Hydroxypropyl Sulfonate, Vanilla Planifolia (Vanilla) Fruit Extract, Water